DRUG LABEL: Unknown
Manufacturer: Ortho Dermatological
Category: prescription | Type: HUMAN PRESCRIPTION DRUG LABELING
Date: 20070417

MONISTAT-DERM
(miconazole nitrate 2%)
Cream

For Topical Use Only

Description:

MONISTAT-DERM (miconazole nitrate 2%) Cream contains miconazole nitrate* 2%, formulated into a water-miscible base consisting of pegoxol 7 stearate, peglicol 5 oleate, mineral oil, benzoic acid, butylated hydroxyanisole and purified water.

*Chemical name: 1-[2,4-dicholoro-B-{(2,5-dichlorobenzyl) oxy} phenethyl] imidazole mononitrate.

Actions:

Miconazole nitrate is a synthetic antifungal agent which inhibits the growth of the common dermatophytes, Trichophyton rubrum, Trichophyton mentagrophytes, and Epidermophyton floccosum, the yeast-like fungus, Candida albicans, and the organism responsible for tinea versicolor (Malassezia furfur).

Indications:

For topical application in the treatment of tinea pedis (athlete's foot), tinea cruris, and tinea corporis caused by Trichophyton rubrum, Trichophyton mentagrophytes, and Epidermophyton floccosum, in the treatment of cutaneous candidiasis (moniliasis), and in the treatment of tinea versicolor.

Contraindications:

MONISTAT-DERM (miconazole nitrate 2%) Cream has no known contraindications.

Precautions:

If a reaction suggesting sensitivity or chemical irritation should occur, use of the medication should be discontinued.

For external use only. Avoid introduction of MONISTAT-DERM Cream into the eyes.

Adverse Reactions:

There have been isolated reports of irritation, burning, maceration, and allergic contact dermatitis associated with the application of MONISTAT-DERM.

Dosage and Administration:

Sufficient MONISTAT-DERM Cream should be applied to cover affected areas twice daily (morning and evening) in patients with tinea pedis, tinea cruris, tinea corporis, and cutaneous candidiasis, and once daily in patients with tinea versicolor. If MONISTAT-DERM Cream is used in intertriginous areas, it should be applied sparingly and smoothed in well to avoid maceration effects.

Early relief of symptoms (2 to 3 days) is experienced by the majority of patients and clinical improvement may be seen fairly soon after treatment is begun; however, Candida infections and tinea cruris and corporis should be treated for two weeks and tinea pedis for one month in order to reduce the possibility of recurrence. If a patient shows no clinical improvement after a month of treatment, the diagnosis should be redetermined. Patients with tinea versicolor usually exhibit clinical and mycological clearing after two weeks of treatment.

How Supplied:

MONISTAT-DERM (miconazole nitrate 2%) Cream containing miconazole nitrate at 2% strength is supplied in 15g, 1 oz. and 3 oz. tubes.

Ortho Dermatological
Division of Ortho-McNeil
Pharmaceutical, Inc.
Skillman, New Jersey 08558

© OMP 2001
Printed in U.S.A.
Revised February 2001
631-10-471-3